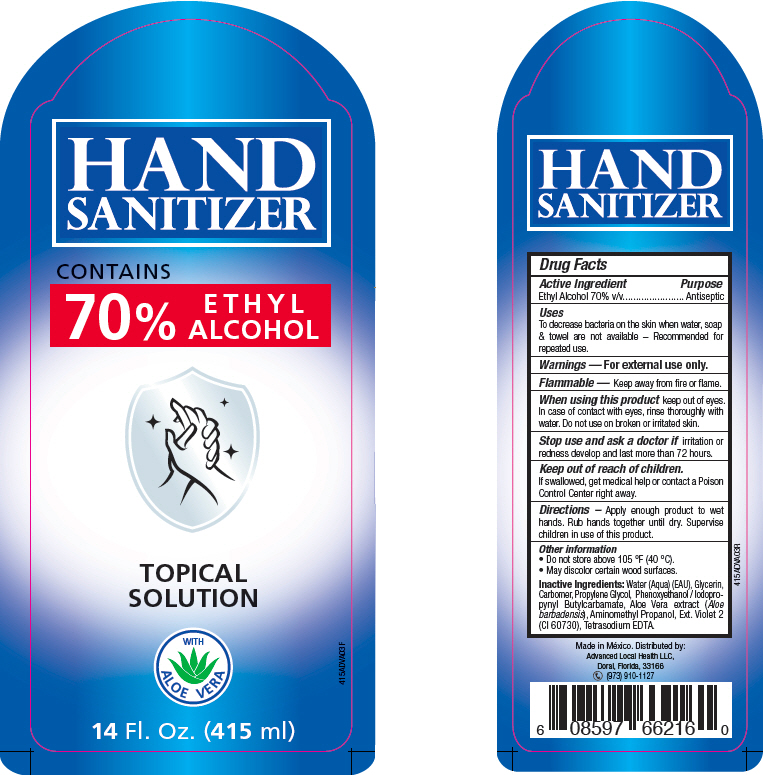 DRUG LABEL: ALH Hand Sanitizer Gen
NDC: 74264-003 | Form: GEL
Manufacturer: Advanced Local Health LLC
Category: otc | Type: HUMAN OTC DRUG LABEL
Date: 20200806

ACTIVE INGREDIENTS: Alcohol 70 mL/100 mL
INACTIVE INGREDIENTS: water; CARBOMER HOMOPOLYMER, UNSPECIFIED TYPE; GLYCERIN; PROPYLENE GLYCOL; PHENOXYETHANOL; AMINOMETHYLPROPANOL; EXT. D&C VIOLET NO. 2; EDETATE SODIUM; ALOE VERA LEAF; IODOPROPYNYL BUTYLCARBAMATE

ALH Hand Sanitizer Gen

Drug Facts

Active Ingredient

Ethyl Alcohol 70% v/v

Purpose

Antiseptic

Uses

To decrease bacteria on the skin when water, soap & towel are not available – Recommended for repeated use.

Warnings

For external use only.

Flammable

Keep away from fire or flame.

When using this product keep out of eyes. In case of contact with eyes, rinse thoroughly with water. Do not use on broken or irritated skin.

Stop use and ask a doctor if irritation or redness develop and last more than 72 hours.

Keep out of reach of children.

If swallowed, get medical help or contact a Poison Control Center right away.

Directions

Apply enough product to wet hands. Rub hands together until dry. Supervise children in use of this product.

Other information

- Do not store above 105 °F (40 °C).
- May discolor certain wood surfaces.

Inactive Ingredients

Water (Aqua) (EAU), Glycerin, Carbomer, Propylene Glycol, Phenoxyethanol / Iodopropynyl Butylcarbamate, Aloe Vera extract (Aloe barbadensis), Aminomethyl Propanol, Ext. Violet 2 (CI 60730), Tetrasodium EDTA.

Distributed by:
Advanced Local Health LLC,
Doral, Florida, 33166

PRINCIPAL DISPLAY PANEL - 415 ml Bottle Label

HAND
SANITIZER

CONTAINS
70%
ETHYL
ALCOHOL

TOPICAL
SOLUTION

WITH
ALOE VERA

14 Fl. Oz. (415 ml)

415ADVA03F